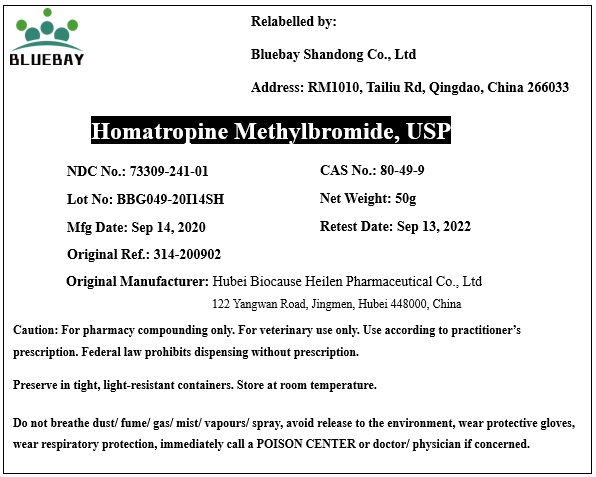 DRUG LABEL: Homatropine Methylbromide
NDC: 73309-241 | Form: POWDER
Manufacturer: BLUEBAY SHANDONG CO.,LTD
Category: other | Type: BULK INGREDIENT
Date: 20210129

ACTIVE INGREDIENTS: HOMATROPINE METHYLBROMIDE 1 g/1 g

Homatropine Methylbromide